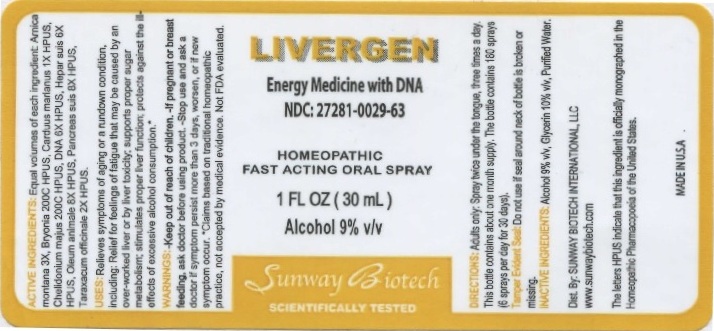 DRUG LABEL: Livergen
NDC: 27281-029 | Form: LIQUID
Manufacturer: Sunway Biotech LLC
Category: homeopathic | Type: HUMAN OTC DRUG LABEL
Date: 20211229

ACTIVE INGREDIENTS: ARNICA MONTANA 3 [hp_X]/30 mL; BRYONIA ALBA ROOT 200 [hp_C]/30 mL; MILK THISTLE 1 [hp_X]/30 mL; CHELIDONIUM MAJUS 200 [hp_C]/30 mL; HERRING SPERM DNA 6 [hp_X]/30 mL; PORK LIVER 6 [hp_X]/30 mL; CERVUS ELAPHUS HORN OIL 8 [hp_X]/30 mL; SUS SCROFA PANCREAS 8 [hp_X]/30 mL; TARAXACUM OFFICINALE 2 [hp_X]/30 mL
INACTIVE INGREDIENTS: ALCOHOL; GLYCERIN; WATER

Livergen

ACTIVE INGREDIENT

ACTIVE INGREDIENTS: Equal volumes of each ingredient: Arnica montana 3X, Bryonia 200C HPUS, Carduus marianus 1X HPUS, Chelidonium majus 200C HPUS, DNA 6X HPUS, Hepar suis 6X HPUS, Oleum animale 8X HPUS, Pancreas suis 8X HPUS, Taraxacum officinale 2X HPUS.

The letters HPUS indicate that this ingredient is officially monographed in the Homeopathic Pharmacopeia of the United States.

INDICATIONS AND USAGE

USES: Relieves symptoms of aging or a rundown condition, including: Relief for feelings of fatigue that may be caused by an over-worked liver or by liver toxixity; supports proper sugar metabolism; stimulates proper liver function; protects against the ill-effects of excessive alcohol consumption.*

*Claims based on traditional homeopathic practice, not accepted by medical evidence. Not FDA evaluated.

WARNINGS

WARNINGS: If pregnant or breast feeding, ask a doctor before using product. Stop use and ask a doctor if symptoms persist more than 3 days, worsen, or if new symptoms occur.

- Keep out of reach of children.

DOSAGE AND ADMINISTRATION

DIRECTIONS: Adults only: Spray twice under the tongue, three times a day. This bottle contains about a 1 month supply. The bottle contains 180 sprays (6 sprays per day for 30 days).

OTHER SAFETY INFORMATION

Tamper Evident Seal: Do not use if seal around neck of bottle is broken or missing.

INACTIVE INGREDIENT

INACTIVE INGREDIENTS: Alcohol 8% v/v, Glycerin 10% v/v, Purified Water.

QUESTIONS

Dist. By: SUNWAY BIOTECH INTERNATIONAL, LLC

www.sunwaybiotech.com

PACKAGE LABEL

LIVERGEN

Energy medicine with DNA

NDC: 27281-029-63

HOMEOPATHIC FAST ACTING ORAL SPRAY

1 FL OZ (30 mL)

Alcohol 9% v/v

Sunway Biotech

SCIENTIFICALLY TESTED

PURPOSE

Energy medicine with DNA